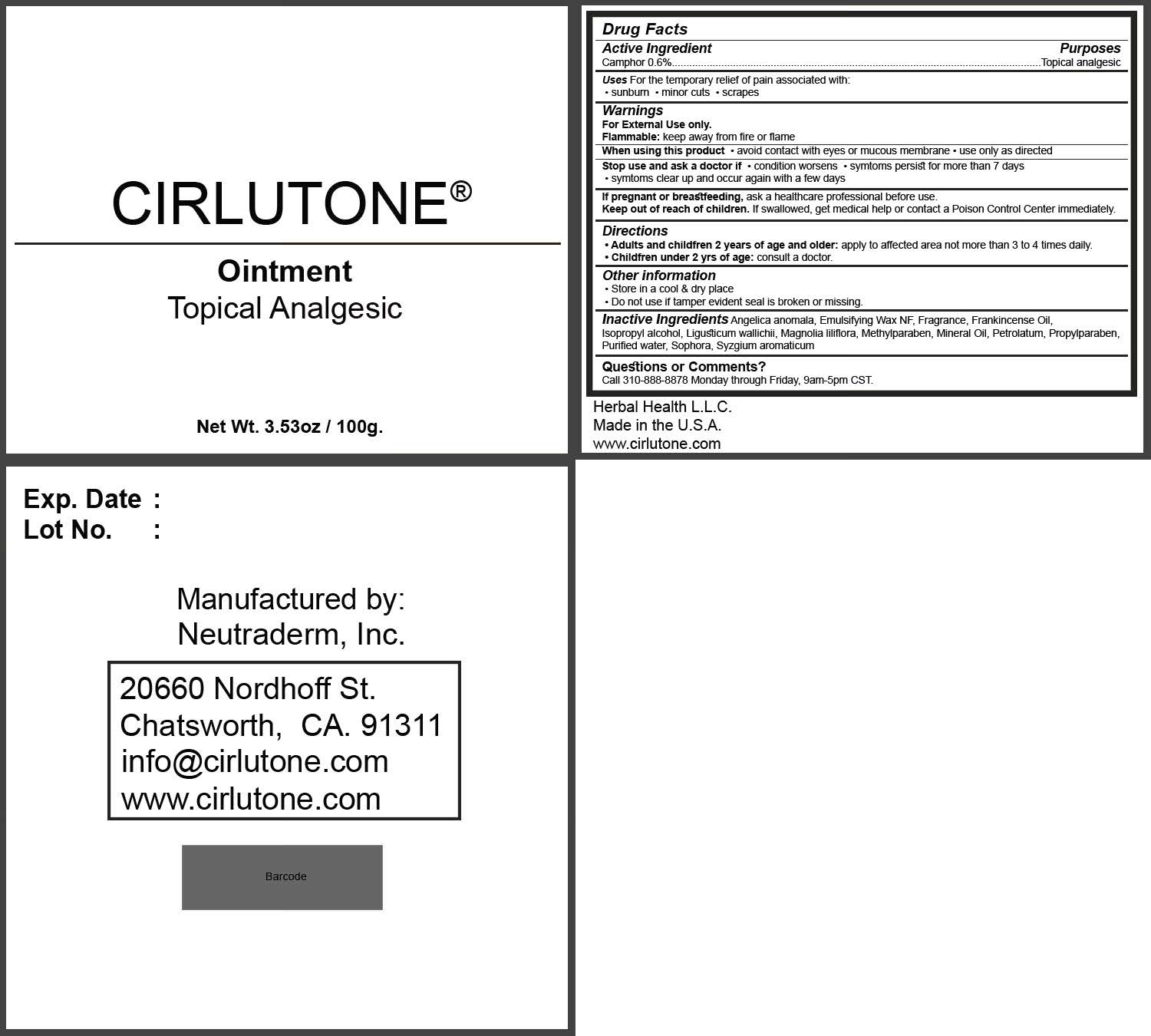 DRUG LABEL: Cirlutone
NDC: 71917-001 | Form: OINTMENT
Manufacturer: Herbal Health LLC
Category: otc | Type: HUMAN OTC DRUG LABEL
Date: 20171206

ACTIVE INGREDIENTS: CAMPHOR (SYNTHETIC) 0.6 g/100 g
INACTIVE INGREDIENTS: ANGELICA ANOMALA WHOLE; WHITE WAX; FRANKINCENSE OIL; ISOPROPYL ALCOHOL; LIGUSTICUM WALLICHII WHOLE; MAGNOLIA LILIIFLORA WHOLE; METHYLPARABEN; MINERAL OIL; PETROLATUM; PROPYLPARABEN; WATER; SOPHORA FLAVESCENS WHOLE; SYZYGIUM AROMATICUM WHOLE

ACTIVE INGREDIENT

Camphor 0.6%

PURPOSE

Camphor 0.6%...............Topical Analgesic

INDICATIONS AND USAGE

For the temporary relief of pain associated with:

- sunburn
- minor cuts
- scrapes

WARNINGS

For External Use only.

Flammable: keep away from fire or flame

When using this product

- avoid contact with eyes or mucous membrane
- use only as directed

Stop use and ask a doctor if

- condition worsens
- symptoms persist for more than 7 days
- symptoms clear up and occur again within a few days

PREGNANCY OR BREAST FEEDING

If pregnant or breastfeeding, ask a healthcare professional before use.

Keep out of reach of children. If swallowed, get medical help or contact a Poison Control Center immediately.

DOSAGE AND ADMINISTRATION

- Adults and children 2 years of age and older: apply to affected area not more than 3 to 4 times daily.
- Children under 2 yrs of age: consult a doctor.

STORAGE AND HANDLING

- Store in a cool & dry place
- Do not use if tamper evident seal is broken or missing

INACTIVE INGREDIENT

Angelica anemala, Emulsifying Wax NF, Fragrance, Frankincense Oil, Isopropyl alcohol, Ligusticum wallichii, Magnolia liliflora, Methylparaben, Mineral Oil, Petrolatum, Propylparaben, Purified Water, Sophora, Syzgium armaticum

QUESTIONS

Call 310-888-8878 Monday through Friday, 9am-5pm CST.

DESCRIPTION

Herbal Health L.L.C.
Made in the U.S.A.
www.cirlutone.com

DESCRIPTION

Exp. Date:

Lot No.:

Manufactured by:

Neutraderm, Inc.

20660 Nordhoff St.

Chatsworth, CA. 91311

info@cirlutone.com

www.cirlutone.com

PACKAGE LABEL

CIRLUTONE

Ointment

Topical Analgesic

Net Wt. 3.53oz/100g.